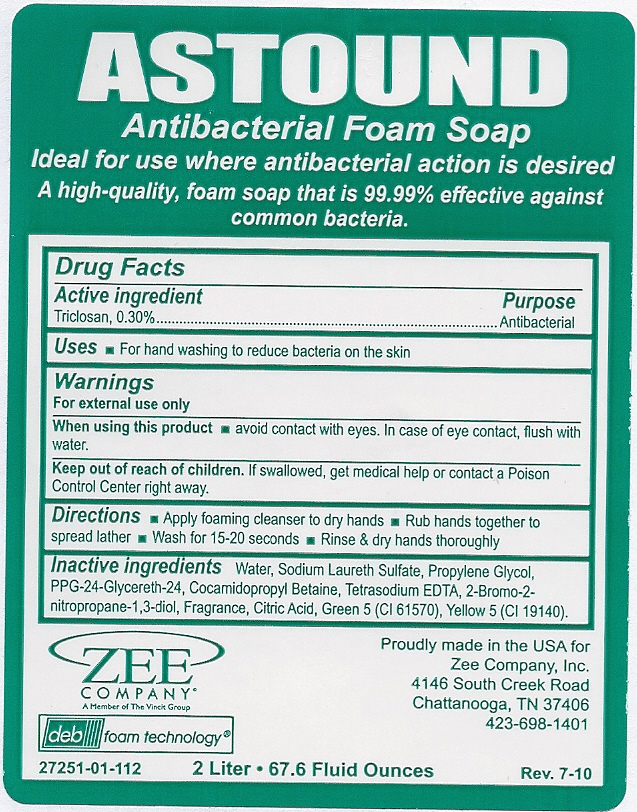 DRUG LABEL: Astound Antibacterial 
NDC: 11084-020 | Form: LIQUID
Manufacturer: Deb USA, Inc.
Category: otc | Type: HUMAN OTC DRUG LABEL
Date: 20110223

ACTIVE INGREDIENTS: Triclosan 0.30 mL/100 mL
INACTIVE INGREDIENTS: WATER; SODIUM LAURETH SULFATE; PROPYLENE GLYCOL; COCAMIDOPROPYL BETAINE; EDETATE SODIUM; ANHYDROUS CITRIC ACID; D&C GREEN NO. 5; FD&C YELLOW NO. 5

Drug Facts

Active ingredient

Triclosan, 0.30%

Purpose

Antibacterial

Uses

For hand washing to reduce bacteria on the skin

Warnings

For external use only

When using this product

Avoid contact with eyes. In case of eye contact, flush with water.

Keep out of reach of children.

If swallowed, get medical help or contact a Poison Control Center right away.

Directions

Apply foaming cleanser to dry hands

Rub hands together to spread lather

Wash for 15-20 seconds

Rinse and dry hands thoroughly

Inactive ingredients

Water, Sodium Laureth Sulfate, Propylene Glycol, PPG-24-Glycereth-24, Cocamidopropyl Betaine, Tetrasodium EDTA, 2-Bromo-2-nitropropane-1, 3-diol, Fragrance, Citric Acid, Green 5 (CI 61570), Yellow 5 (CI 19140).

PACKAGE LABEL

Astound

Antibacterial Foam Soap

Ideal for use where antibacterial action is desired

A high-quality, foam soap that is 99.99% effective against common bacteria.

ZEE Company

deb foam technology

Proudly made in the USA for Zee Company, Inc.

27251-01-112

2 Liter

67.6 Fluid Ounces

Rev. 7-10